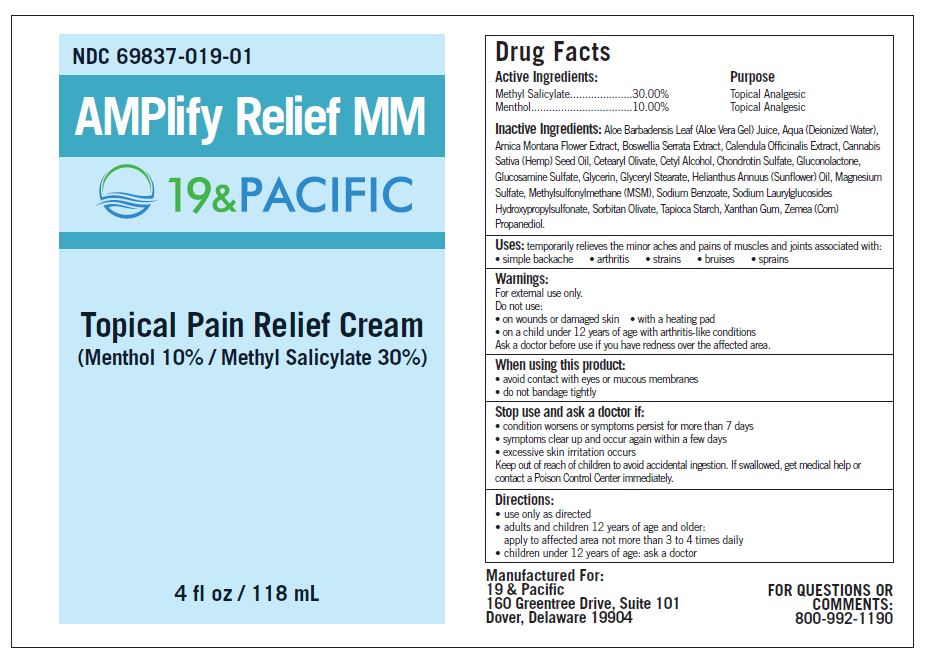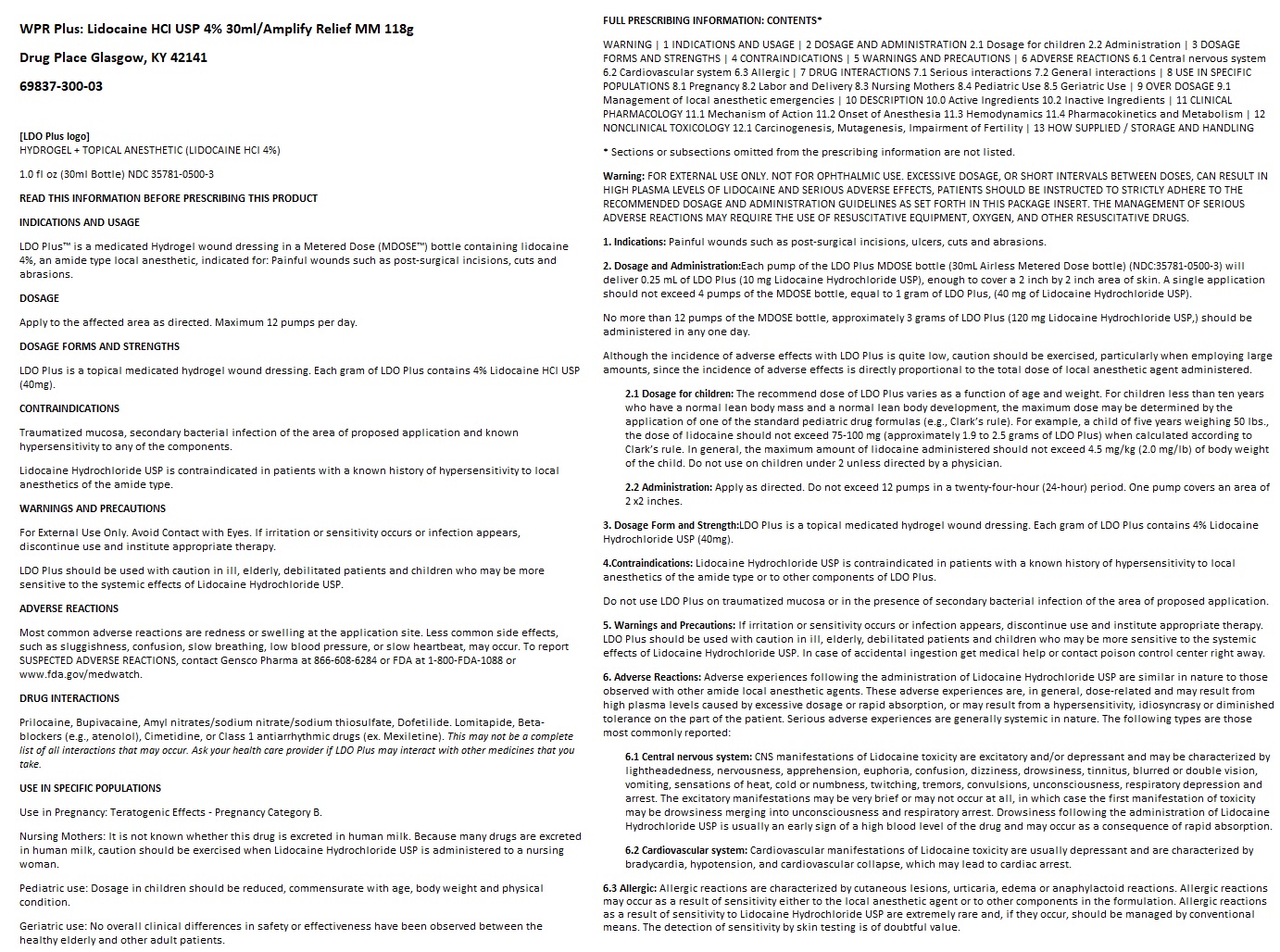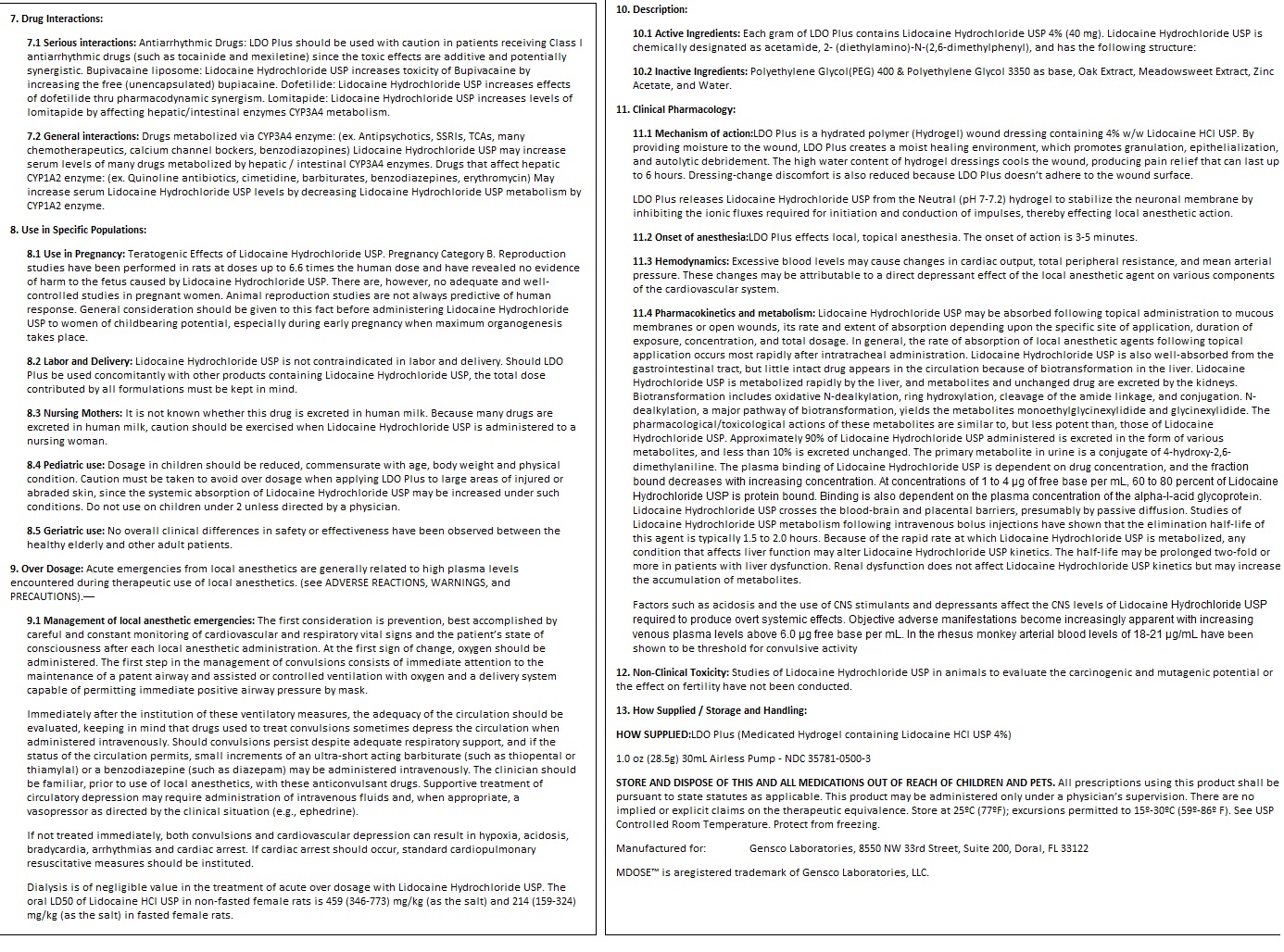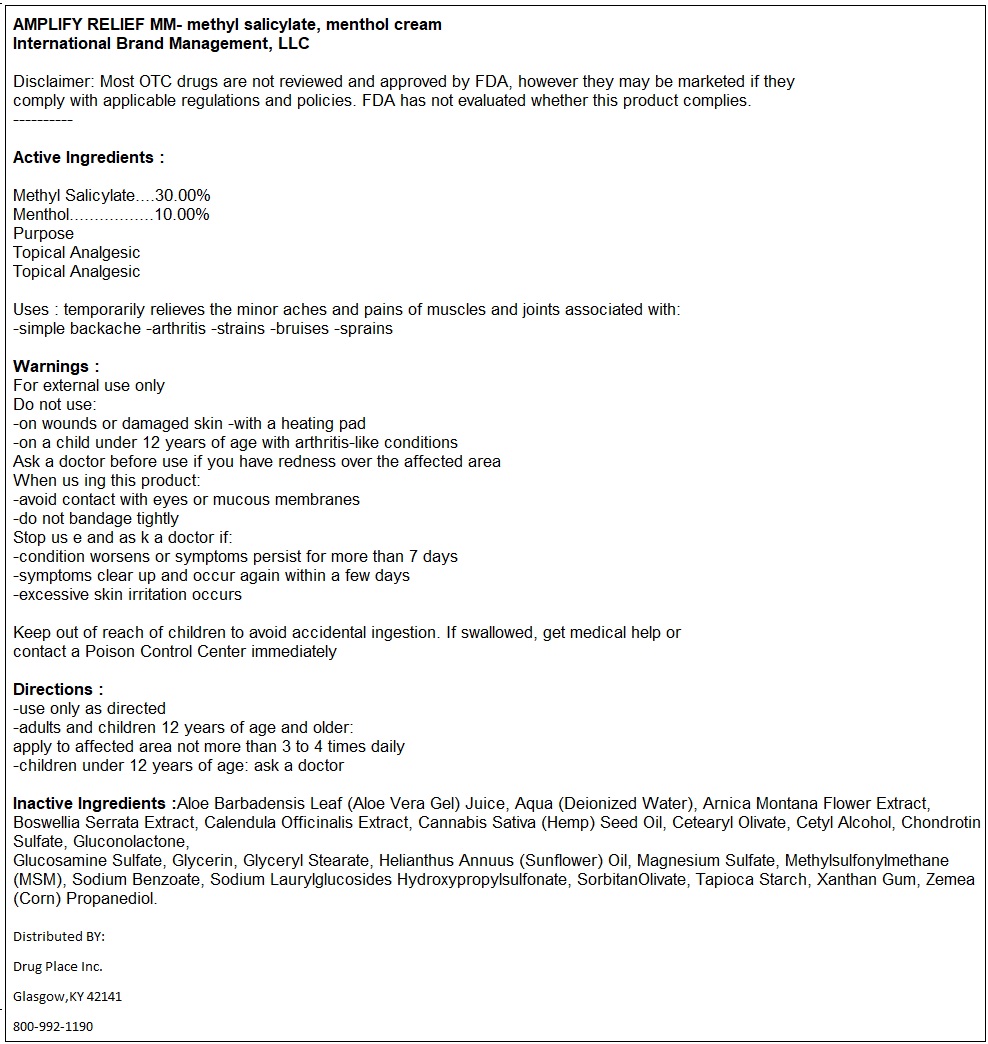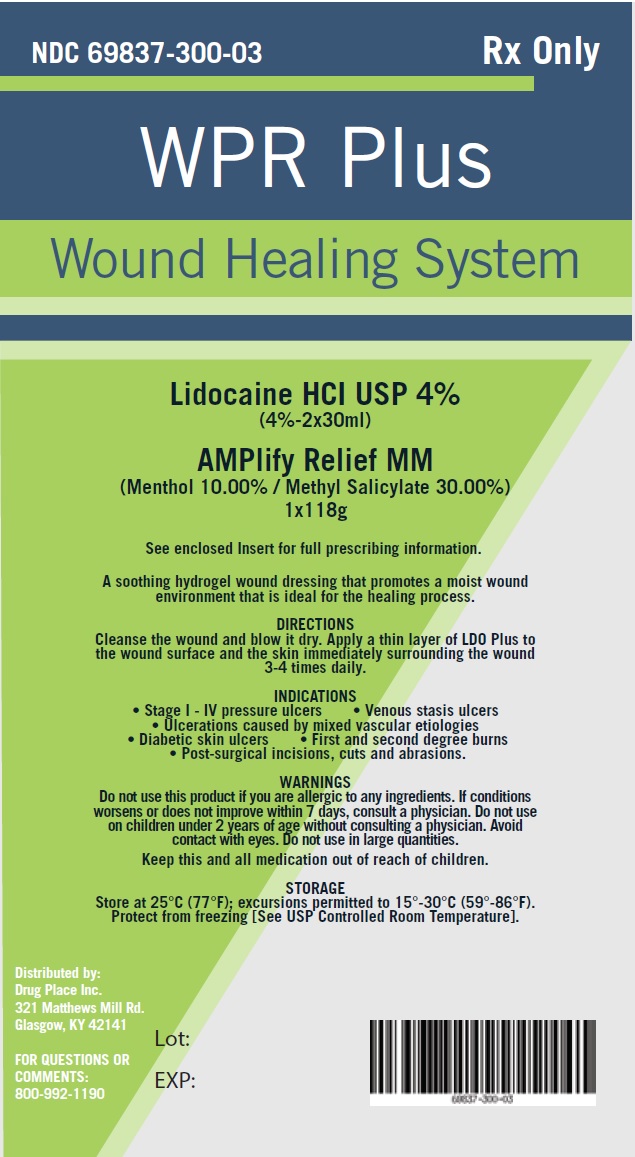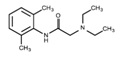 DRUG LABEL: WPR Plus
NDC: 69837-301 | Form: KIT | Route: TOPICAL
Manufacturer: International Brand Management, LLC
Category: otc | Type: HUMAN OTC DRUG LABEL
Date: 20180717

ACTIVE INGREDIENTS: METHYL SALICYLATE 3 g/10 g; MENTHOL 1 g/10 g; LIDOCAINE 40 mg/1 g
INACTIVE INGREDIENTS: ALOE VERA LEAF; WATER; ARNICA MONTANA FLOWER; INDIAN FRANKINCENSE; HEMP; CETEARYL OLIVATE; CETYL ALCOHOL; GLUCONOLACTONE; GLUCOSAMINE SULFATE; GLYCERIN; GLYCERYL MONOSTEARATE; HELIANTHUS ANNUUS FLOWERING TOP; MAGNESIUM SULFATE, UNSPECIFIED FORM; DIMETHYL SULFONE; SODIUM BENZOATE; SORBITAN OLIVATE; STARCH, TAPIOCA; XANTHAN GUM; CORN; FILIPENDULA ULMARIA FLOWER; QUERCUS ALBA WOOD; POLYETHYLENE GLYCOL 400; POLYETHYLENE GLYCOL 3350; WATER; ZINC ACETATE

WPR Plus

INDICATIONS AND USAGE

LDO Plus™ is a medicated Hydrogel wound dressing in a Metered Dose (MDOSE™) bottle containing lidocaine 4%, an amide type local anesthetic, indicated for: Painful wounds such as post-surgical incisions, cuts and abrasions.

DOSAGE
Apply to the affected area as directed. Maximum 12 pumps per day.

DOSAGE FORMS AND STRENGTHS

LDO Plus is a topical medicated hydrogel wound dressing. Each gram of LDO Plus contains 4% Lidocaine HCl USP (40mg).

CONTRAINDICATIONS

Traumatized mucosa, secondary bacterial infection of the area of proposed application and known hypersensitivity to any of the components.
Lidocaine Hydrochloride USP is contraindicated in patients with a known history of hypersensitivity to local anesthetics of the amide type.

WARNINGS AND PRECAUTIONS

For External Use Only. Avoid Contact with Eyes. If irritation or sensitivity occurs or infection appears, discontinue use and institute appropriate therapy.
LDO Plus should be used with caution in ill, elderly, debilitated patients and children who may be more sensitive to the systemic effects of Lidocaine Hydrochloride USP.

ADVERSE REACTIONS

Most common adverse reactions are redness or swelling at the application site. Less common side effects, such as sluggishness, confusion, slow breathing, low blood pressure, or slow heartbeat, may occur. To report SUSPECTED ADVERSE REACTIONS, contact Gensco Pharma at 866-608-6284 or FDA at 1-800-FDA-1088 or www.fda.gov/medwatch.

DRUG INTERACTIONS

Prilocaine, Bupivacaine, Amyl nitrates/sodium nitrate/sodium thiosulfate, Dofetilide. Lomitapide, Beta-blockers (e.g., atenolol), Cimetidine, or Class 1 antiarrhythmic drugs (ex. Mexiletine). This may not be a complete list of all interactions that may occur. Ask your health care provider if LDO Plus may interact with other medicines that you take.

USE IN SPECIFIC POPULATIONS

Use in Pregnancy: Teratogenic Effects - Pregnancy Category B.
Nursing Mothers: It is not known whether this drug is excreted in human milk. Because many drugs are excreted in human milk, caution should be exercised when Lidocaine Hydrochloride USP is administered to a nursing woman.
Pediatric use: Dosage in children should be reduced, commensurate with age, body weight and physical condition.
Geriatric use: No overall clinical differences in safety or effectiveness have been observed between the healthy elderly and other adult patients.

FULL PRESCRIBING INFORMATION: CONTENTS*

WARNING | 1 INDICATIONS AND USAGE | 2 DOSAGE AND ADMINISTRATION 2.1 Dosage for children 2.2 Administration | 3 DOSAGE FORMS AND STRENGTHS | 4 CONTRAINDICATIONS | 5 WARNINGS AND PRECAUTIONS | 6 ADVERSE REACTIONS 6.1 Central nervous system 6.2 Cardiovascular system 6.3 Allergic | 7 DRUG INTERACTIONS 7.1 Serious interactions 7.2 General interactions | 8 USE IN SPECIFIC POPULATIONS 8.1 Pregnancy 8.2 Labor and Delivery 8.3 Nursing Mothers 8.4 Pediatric Use 8.5 Geriatric Use | 9 OVER DOSAGE 9.1 Management of local anesthetic emergencies | 10 DESCRIPTION 10.0 Active Ingredients 10.2 Inactive Ingredients | 11 CLINICAL PHARMACOLOGY 11.1 Mechanism of Action 11.2 Onset of Anesthesia 11.3 Hemodynamics 11.4 Pharmacokinetics and Metabolism | 12 NONCLINICAL TOXICOLOGY 12.1 Carcinogenesis, Mutagenesis, Impairment of Fertility | 13 HOW SUPPLIED / STORAGE AND HANDLING
* Sections or subsections omitted from the prescribing information are not listed.

Warning:

FOR EXTERNAL USE ONLY. NOT FOR OPHTHALMIC USE. EXCESSIVE DOSAGE, OR SHORT INTERVALS BETWEEN DOSES, CAN RESULT IN HIGH PLASMA LEVELS OF LIDOCAINE AND SERIOUS ADVERSE EFFECTS, PATIENTS SHOULD BE INSTRUCTED TO STRICTLY ADHERE TO THE RECOMMENDED DOSAGE AND ADMINISTRATION GUIDELINES AS SET FORTH IN THIS PACKAGE INSERT. THE MANAGEMENT OF SERIOUS ADVERSE REACTIONS MAY REQUIRE THE USE OF RESUSCITATIVE EQUIPMENT, OXYGEN, AND OTHER RESUSCITATIVE DRUGS.

1. Indications

Painful wounds such as post-surgical incisions, ulcers, cuts and abrasions.

2. Dosage and Administration:

Each pump of the LDO Plus MDOSE bottle (30mL Airless Metered Dose bottle) (NDC:35781-0500-3) will deliver 0.25 mL of LDO Plus (10 mg Lidocaine Hydrochloride USP), enough to cover a 2 inch by 2 inch area of skin. A single application should not exceed 4 pumps of the MDOSE bottle, equal to 1 gram of LDO Plus, (40 mg of Lidocaine Hydrochloride USP).
No more than 12 pumps of the MDOSE bottle, approximately 3 grams of LDO Plus (120 mg Lidocaine Hydrochloride USP,) should be administered in any one day.
Although the incidence of adverse effects with LDO Plus is quite low, caution should be exercised, particularly when employing large amounts, since the incidence of adverse effects is directly proportional to the total dose of local anesthetic agent administered.

2.1 Dosage for children:

The recommend dose of LDO Plus varies as a function of age and weight. For children less than ten years who have a normal lean body mass and a normal lean body development, the maximum dose may be determined by the application of one of the standard pediatric drug formulas (e.g., Clark’s rule). For example, a child of five years weighing 50 lbs., the dose of lidocaine should not exceed 75-100 mg (approximately 1.9 to 2.5 grams of LDO Plus) when calculated according to Clark’s rule. In general, the maximum amount of lidocaine administered should not exceed 4.5 mg/kg (2.0 mg/lb) of body weight of the child. Do not use on children under 2 unless directed by a physician.

2.2 Administration:

Apply as directed. Do not exceed 12 pumps in a twenty-four-hour (24-hour) period. One pump covers an area of 2 x2 inches.

3. Dosage Form and Strength:

LDO Plus is a topical medicated hydrogel wound dressing. Each gram of LDO Plus contains 4% Lidocaine Hydrochloride USP (40mg).

4.Contraindications:

Lidocaine Hydrochloride USP is contraindicated in patients with a known history of hypersensitivity to local anesthetics of the amide type or to other components of LDO Plus.
Do not use LDO Plus on traumatized mucosa or in the presence of secondary bacterial infection of the area of proposed application.

5. Warnings and Precautions:

If irritation or sensitivity occurs or infection appears, discontinue use and institute appropriate therapy. LDO Plus should be used with caution in ill, elderly, debilitated patients and children who may be more sensitive to the systemic effects of Lidocaine Hydrochloride USP. In case of accidental ingestion get medical help or contact poison control center right away.

6. Adverse Reactions:

Adverse experiences following the administration of Lidocaine Hydrochloride USP are similar in nature to those observed with other amide local anesthetic agents. These adverse experiences are, in general, dose-related and may result from high plasma levels caused by excessive dosage or rapid absorption, or may result from a hypersensitivity, idiosyncrasy or diminished tolerance on the part of the patient. Serious adverse experiences are generally systemic in nature. The following types are those most commonly reported:

6.1 Central nervous system:

CNS manifestations of Lidocaine toxicity are excitatory and/or depressant and may be characterized by lightheadedness, nervousness, apprehension, euphoria, confusion, dizziness, drowsiness, tinnitus, blurred or double vision, vomiting, sensations of heat, cold or numbness, twitching, tremors, convulsions, unconsciousness, respiratory depression and arrest. The excitatory manifestations may be very brief or may not occur at all, in which case the first manifestation of toxicity may be drowsiness merging into unconsciousness and respiratory arrest. Drowsiness following the administration of Lidocaine Hydrochloride USP is usually an early sign of a high blood level of the drug and may occur as a consequence of rapid absorption.

6.2 Cardiovascular system:

Cardiovascular manifestations of Lidocaine toxicity are usually depressant and are characterized by bradycardia, hypotension, and cardiovascular collapse, which may lead to cardiac arrest.

6.3 Allergic:

Allergic reactions are characterized by cutaneous lesions, urticaria, edema or anaphylactoid reactions. Allergic reactions may occur as a result of sensitivity either to the local anesthetic agent or to other components in the formulation. Allergic reactions as a result of sensitivity to Lidocaine Hydrochloride USP are extremely rare and, if they occur, should be managed by conventional means. The detection of sensitivity by skin testing is of doubtful value.

7. Drug Interactions:

7.1 Serious interactions: Antiarrhythmic Drugs: LDO Plus should be used with caution in patients receiving Class I antiarrhythmic drugs (such as tocainide and mexiletine) since the toxic effects are additive and potentially synergistic. Bupivacaine liposome: Lidocaine Hydrochloride USP increases toxicity of Bupivacaine by increasing the free (unencapsulated) bupiacaine. Dofetilide: Lidocaine Hydrochloride USP increases effects of dofetilide thru pharmacodynamic synergism. Lomitapide: Lidocaine Hydrochloride USP increases levels of lomitapide by affecting hepatic/intestinal enzymes CYP3A4 metabolism.

7.2 General interactions:

Drugs metabolized via CYP3A4 enzyme: (ex. Antipsychotics, SSRIs, TCAs, many chemotherapeutics, calcium channel bockers, benzodiazopines) Lidocaine Hydrochloride USP may increase serum levels of many drugs metabolized by hepatic / intestinal CYP3A4 enzymes. Drugs that affect hepatic CYP1A2 enzyme: (ex. Quinoline antibiotics, cimetidine, barbiturates, benzodiazepines, erythromycin) May increase serum Lidocaine Hydrochloride USP levels by decreasing Lidocaine Hydrochloride USP metabolism by CYP1A2 enzyme.

8. Use in Specific Populations:

8.1 Use in Pregnancy: Teratogenic Effects of Lidocaine Hydrochloride USP. Pregnancy Category B. Reproduction studies have been performed in rats at doses up to 6.6 times the human dose and have revealed no evidence of harm to the fetus caused by Lidocaine Hydrochloride USP. There are, however, no adequate and well-controlled studies in pregnant women. Animal reproduction studies are not always predictive of human response. General consideration should be given to this fact before administering Lidocaine Hydrochloride USP to women of childbearing potential, especially during early pregnancy when maximum organogenesis takes place.

8.2 Labor and Delivery:

Lidocaine Hydrochloride USP is not contraindicated in labor and delivery. Should LDO Plus be used concomitantly with other products containing Lidocaine Hydrochloride USP, the total dose contributed by all formulations must be kept in mind.

8.3 Nursing Mothers:

It is not known whether this drug is excreted in human milk. Because many drugs are excreted in human milk, caution should be exercised when Lidocaine Hydrochloride USP is administered to a nursing woman.

8.4 Pediatric use:

Dosage in children should be reduced, commensurate with age, body weight and physical condition. Caution must be taken to avoid over dosage when applying LDO Plus to large areas of injured or abraded skin, since the systemic absorption of Lidocaine Hydrochloride USP may be increased under such conditions. Do not use on children under 2 unless directed by a physician

8.5 Geriatric use:

No overall clinical differences in safety or effectiveness have been observed between the healthy elderly and other adult patients.

9. Over Dosage:

Acute emergencies from local anesthetics are generally related to high plasma levels encountered during therapeutic use of local anesthetics. (see ADVERSE REACTIONS, WARNINGS, and PRECAUTIONS).

9.1 Management of local anesthetic emergencies:

The first consideration is prevention, best accomplished by careful and constant monitoring of cardiovascular and respiratory vital signs and the patient’s state of consciousness after each local anesthetic administration. At the first sign of change, oxygen should be administered. The first step in the management of convulsions consists of immediate attention to the maintenance of a patent airway and assisted or controlled ventilation with oxygen and a delivery system capable of permitting immediate positive airway pressure by mask.
Immediately after the institution of these ventilatory measures, the adequacy of the circulation should be evaluated, keeping in mind that drugs used to treat convulsions sometimes depress the circulation when administered intravenously. Should convulsions persist despite adequate respiratory support, and if the status of the circulation permits, small increments of an ultra-short acting barbiturate (such as thiopental or thiamylal) or a benzodiazepine (such as diazepam) may be administered intravenously. The clinician should be familiar, prior to use of local anesthetics, with these anticonvulsant drugs. Supportive treatment of circulatory depression may require administration of intravenous fluids and, when appropriate, a vasopressor as directed by the clinical situation (e.g., ephedrine).
If not treated immediately, both convulsions and cardiovascular depression can result in hypoxia, acidosis, bradycardia, arrhythmias and cardiac arrest. If cardiac arrest should occur, standard cardiopulmonary resuscitative measures should be instituted.
Dialysis is of negligible value in the treatment of acute over dosage with Lidocaine Hydrochloride USP. The oral LD50 of Lidocaine HCI USP in non-fasted female rats is 459 (346-773) mg/kg (as the salt) and 214 (159-324) mg/kg (as the salt) in fasted female rats.

10. Description:

10.1 Active Ingredients: Each gram of LDO Plus contains Lidocaine Hydrochloride USP 4% (40 mg). Lidocaine Hydrochloride USP is chemically designated as acetamide, 2- (diethylamino)-N-(2,6-dimethylphenyl), and has the following structure:

10.2 Inactive Ingredients:

Polyethylene Glycol(PEG) 400 & Polyethylene Glycol 3350 as base, Oak Extract, Meadowsweet Extract, Zinc Acetate, and Water.

11. Clinical Pharmacology:

11.1 Mechanism of action:LDO Plus is a hydrated polymer (Hydrogel) wound dressing containing 4% w/w Lidocaine HCl USP. By providing moisture to the wound, LDO Plus creates a moist healing environment, which promotes granulation, epithelialization, and autolytic debridement. The high water content of hydrogel dressings cools the wound, producing pain relief that can last up to 6 hours. Dressing-change discomfort is also reduced because LDO Plus doesn’t adhere to the wound surface.
LDO Plus releases Lidocaine Hydrochloride USP from the Neutral (pH 7-7.2) hydrogel to stabilize the neuronal membrane by inhibiting the ionic fluxes required for initiation and conduction of impulses, thereby effecting local anesthetic action.

11.2 Onset of anesthesia:

LDO Plus effects local, topical anesthesia. The onset of action is 3-5 minutes.

11.3 Hemodynamics:

Excessive blood levels may cause changes in cardiac output, total peripheral resistance, and mean arterial pressure. These changes may be attributable to a direct depressant effect of the local anesthetic agent on various components of the cardiovascular system.

11.4 Pharmacokinetics and metabolism:

Lidocaine Hydrochloride USP may be absorbed following topical administration to mucous membranes or open wounds, its rate and extent of absorption depending upon the specific site of application, duration of exposure, concentration, and total dosage. In general, the rate of absorption of local anesthetic agents following topical application occurs most rapidly after intratracheal administration. Lidocaine Hydrochloride USP is also well-absorbed from the gastrointestinal tract, but little intact drug appears in the circulation because of biotransformation in the liver. Lidocaine Hydrochloride USP is metabolized rapidly by the liver, and metabolites and unchanged drug are excreted by the kidneys. Biotransformation includes oxidative N-dealkylation, ring hydroxylation, cleavage of the amide linkage, and conjugation. N-dealkylation, a major pathway of biotransformation, yields the metabolites monoethylglycinexylidide and glycinexylidide. The pharmacological/toxicological actions of these metabolites are similar to, but less potent than, those of Lidocaine Hydrochloride USP. Approximately 90% of Lidocaine Hydrochloride USP administered is excreted in the form of various metabolites, and less than 10% is excreted unchanged. The primary metabolite in urine is a conjugate of 4-hydroxy-2,6-dimethylaniline. The plasma binding of Lidocaine Hydrochloride USP is dependent on drug concentration, and the fraction bound decreases with increasing concentration. At concentrations of 1 to 4 μg of free base per mL, 60 to 80 percent of Lidocaine Hydrochloride USP is protein bound. Binding is also dependent on the plasma concentration of the alpha-l-acid glycoprotein. Lidocaine Hydrochloride USP crosses the blood-brain and placental barriers, presumably by passive diffusion. Studies of Lidocaine Hydrochloride USP metabolism following intravenous bolus injections have shown that the elimination half-life of this agent is typically 1.5 to 2.0 hours. Because of the rapid rate at which Lidocaine Hydrochloride USP is metabolized, any condition that affects liver function may alter Lidocaine Hydrochloride USP kinetics. The half-life may be prolonged two-fold or more in patients with liver dysfunction. Renal dysfunction does not affect Lidocaine Hydrochloride USP kinetics but may increase the accumulation of metabolites.

12. Non-Clinical Toxicity:

Studies of Lidocaine Hydrochloride USP in animals to evaluate the carcinogenic and mutagenic potential or the effect on fertility have not been conducted.

13. How Supplied / Storage and Handling:

HOW SUPPLIED:LDO Plus (Medicated Hydrogel containing Lidocaine HCl USP 4%)
1.0 oz (28.5g) 30mL Airless Pump - NDC 35781-0500-3
STORE AND DISPOSE OF THIS AND ALL MEDICATIONS OUT OF REACH OF CHILDREN AND PETS. All prescriptions using this product shall be pursuant to state statutes as applicable. This product may be administered only under a physician’s supervision. There are no implied or explicit claims on the therapeutic equivalence. Store at 25ºC (77ºF); excursions permitted to 15º-30ºC (59º-86º F). See USP Controlled Room Temperature. Protect from freezing.
Manufactured for: Gensco Laboratories, 8550 NW 33rd Street, Suite 200, Doral, FL 33122
MDOSE™ is aregistered trademark of Gensco Laboratories, LLC.

Active Ingredients :

Methyl Salicylate....30.00%
Menthol.................10.00%

Purpose

Topical Analgesic

Uses:

temporarily relieves the minor aches and pains of muscles and joints associated with:
-simple backache -arthritis -strains -bruises -sprains

Warnings:

For external use only

Do not use:

- on wounds or damaged skin -with a heating pad
- on a child under 12 years of age with arthritis-like conditions

Ask a doctor before use

if you have redness over the affected area

When using this product:

- avoid contact with eyes or mucous membranes
- do not bandage tightly

Stop use and ask a doctor if:

- condition worsens or symptoms persist for more than 7 days
- symptoms clear up and occur again within a few days
- excessive skin irritation occurs

Keep out of reach of children

to avoid accidental ingestion. If swallowed, get medical help or contact a Poison Control Center immediately

Directions:

- use only as directed
- adults and children 12 years of age and older:
apply to affected area not more than 3 to 4 times daily
- children under 12 years of age: ask a doctor

Inactive ingredients

Aloe Barbadensis Leaf (Aloe Vera Gel) Juice, Aqua (Deionized Water), Arnica Montana Flower Extract, Boswellia Serrata Extract, Calendula Officinalis Extract, Cannabis Sativa (Hemp) Seed Oil, Cetearyl Olivate, Cetyl Alcohol, Chondrotin Sulfate, Gluconolactone, Glucosamine Sulfate, Glycerin, Glyceryl Stearate, Helianthus Annuus (Sunflower) Oil, Magnesium Sulfate, Methylsulfonylmethane (MSM), Sodium Benzoate, Sodium Laurylglucosides Hydroxypropylsulfonate, SorbitanOlivate, Tapioca Starch, Xanthan Gum, Zemea (Corn) Propanediol.